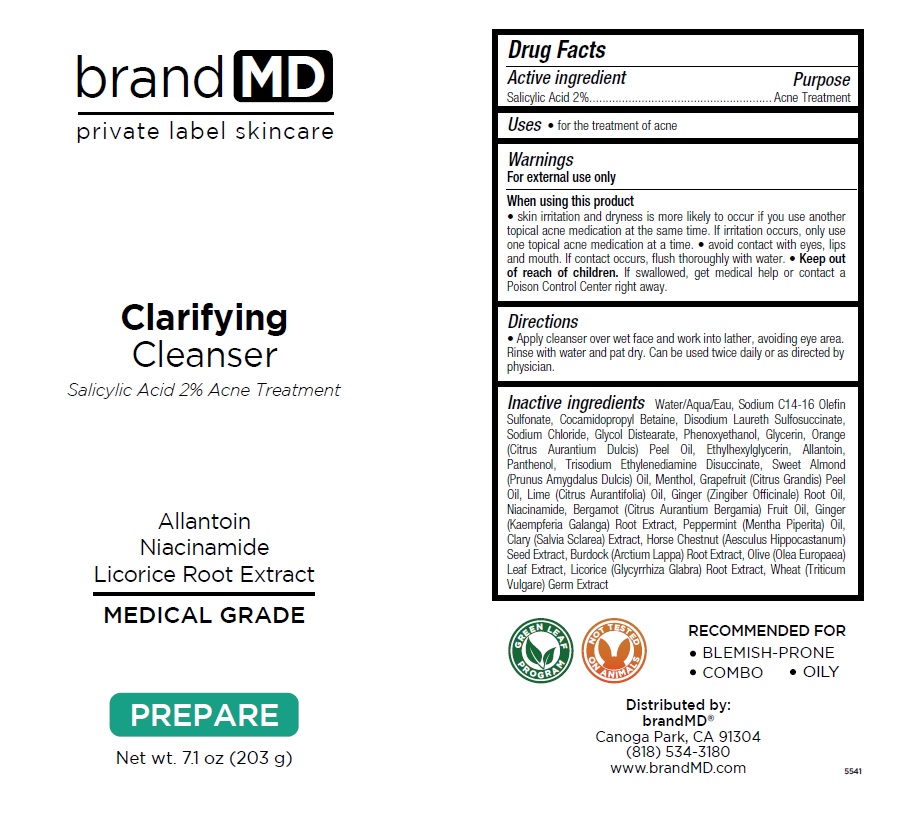 DRUG LABEL: Clarifying Cleanser
NDC: 72957-011 | Form: GEL
Manufacturer: Private Label Skin Care
Category: otc | Type: HUMAN OTC DRUG LABEL
Date: 20250226

ACTIVE INGREDIENTS: SALICYLIC ACID 2 g/100 g
INACTIVE INGREDIENTS: WATER; SODIUM C14-16 OLEFIN SULFONATE; COCAMIDOPROPYL BETAINE; DISODIUM LAURETH SULFOSUCCINATE; SODIUM CHLORIDE; GLYCOL DISTEARATE; PHENOXYETHANOL; GLYCERIN; ORANGE OIL, COLD PRESSED; ETHYLHEXYLGLYCERIN; ALLANTOIN; PANTHENOL; TRISODIUM ETHYLENEDIAMINE DISUCCINATE; ALMOND OIL; MENTHOL, UNSPECIFIED FORM; CITRUS MAXIMA FRUIT RIND OIL; LIME OIL, COLD PRESSED; GINGER OIL; NIACINAMIDE; BERGAMOT OIL; KAEMPFERIA GALANGA ROOT; PEPPERMINT OIL; CLARY SAGE; HORSE CHESTNUT; ARCTIUM LAPPA ROOT; OLEA EUROPAEA (OLIVE) LEAF; LICORICE; WHEAT GERM

Clarifying Cleanser

Active ingredient

Salicylic Acid 2%

Purpose

Acne Treatment

Uses

• for the treatment of acne

Warnings

For external use only

When using this product
• skin irritation and dryness is more likely to occur if you use another topical acne medication at the same time. If irritation occurs, only use one topical acne medication at a time. • avoid contact with eyes, lips and mouth. If contact occurs, flush thoroughly with water.

• Keep out of reach of children. If swallowed, get medical help or contact a Poison Control Center right away.

Directions

• Apply cleanser over wet face and work into lather, avoiding eye area. Rinse with water and pat dry. Can be used twice daily or as directed by physician.

Inactive ingredients

Water/Aqua/Eau, Sodium C14-16 Olefin Sulfonate, Cocamidopropyl Betaine, Disodium Laureth Sulfosuccinate, Sodium Chloride, Glycol Distearate, Phenoxyethanol, Glycerin, Orange (Citrus Aurantium Dulcis) Peel Oil, Ethylhexylglycerin, Allantoin, Panthenol, Trisodium Ethylenediamine Disuccinate, Sweet Almond (Prunus Amygdalus Dulcis) Oil, Menthol, Grapefruit (Citrus Grandis) Peel Oil, Lime (Citrus Aurantifolia) Oil, Ginger (Zingiber Officinale) Root Oil, Niacinamide, Bergamot (Citrus Aurantium Bergamia) Fruit Oil, Ginger (Kaempferia Galanga) Root Extract, Peppermint (Mentha Piperita) Oil, Clary (Salvia Sclarea) Extract, Horse Chestnut (Aesculus Hippocastanum) Seed Extract, Burdock (Arctium Lappa) Root Extract, Olive (Olea Europaea) Leaf Extract, Licorice (Glycyrrhiza Glabra) Root Extract, Wheat (Triticum Vulgare) Germ Extract

brand MD

Allantoin
Niacinamide
Licorice Root Extract

MEDICAL GRADE

PREPARE

RECOMMENDED FOR
• BLEMISH-PRONE
• COMBO • OILY

GREEN LEAF PROGRAM

NOT TESTED ON ANIMALS

Distributed by:
brandMD®
Canoga Park, CA 91304
(818) 534-3180
www.brandMD.com